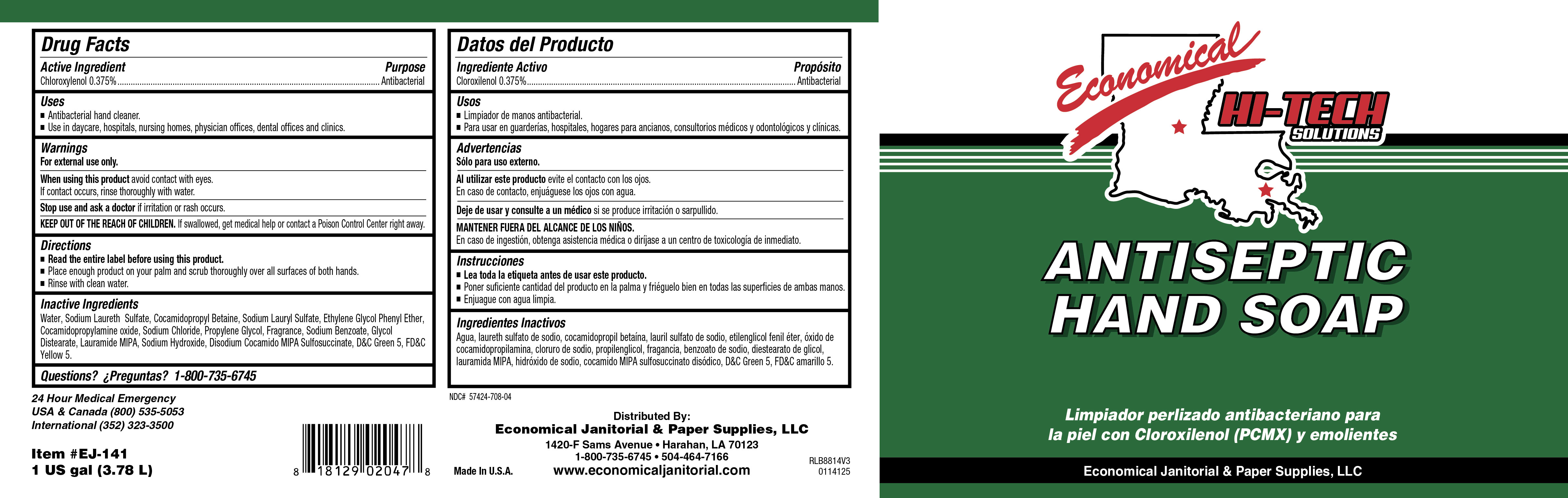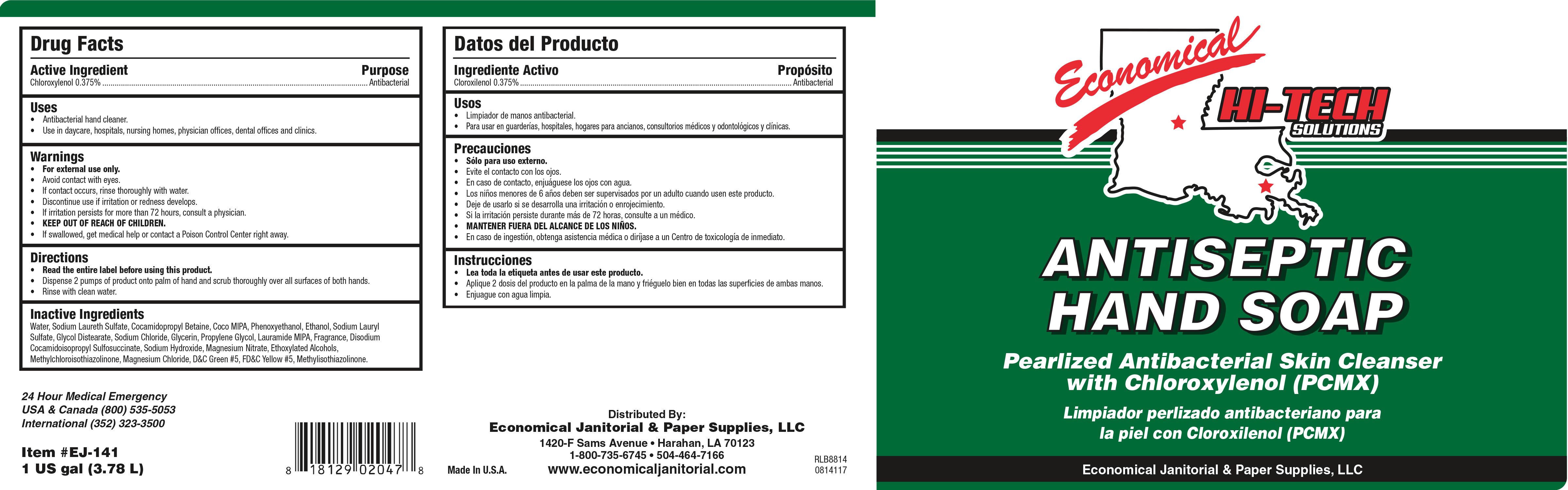 DRUG LABEL: Hi-Tech
NDC: 57424-708 | Form: SOAP
Manufacturer: Economical Janitorial Supplies
Category: otc | Type: HUMAN OTC DRUG LABEL
Date: 20241118

ACTIVE INGREDIENTS: CHLOROXYLENOL 3.75 mg/1 mL
INACTIVE INGREDIENTS: .BETA.-CITRONELLOL, (+/-)-; 3-(3,4-METHYLENEDIOXYPHENYL)-2-METHYLPROPANAL; .GAMMA.-UNDECALACTONE; ETHYLENE BRASSYLATE; LAURIC ISOPROPANOLAMIDE; SODIUM CARBONATE; GLYCOL DISTEARATE; ETHYLENE OXIDE; LINALOOL, (+/-)-; D&C GREEN NO. 5; FD&C YELLOW NO. 5; SODIUM HYDROXIDE; DIHYDROMYRCENOL; SODIUM ALUMINIUM SILICATE; WATER; SODIUM LAURYL SULFATE; COCAMIDOPROPYL BETAINE; PROPYLENE GLYCOL; TRIBASIC CALCIUM PHOSPHATE; HEXYL SALICYLATE; HEXAHYDRO-4,7-METHANOINDEN-6-YL PROPIONATE; VERDYL ACETATE; 2,6-DIMETHYL-5-HEPTENAL; .ALPHA.-AMYLCINNAMALDEHYDE; 2-TERT-BUTYLCYCLOHEXYL ACETATE; 2-ISOBUTYL-4-METHYLTETRAHYDROPYRAN-4-OL; SODIUM CHLORIDE; .ALPHA.-HEXYLCINNAMALDEHYDE; PHENYLETHYL ALCOHOL; 1-(2,3,8,8-TETRAMETHYL-1,2,3,4,5,6,7,8-OCTAHYDRONAPHTHALEN-2-YL)ETHANONE; 4-ACETOXY-3-PENTYLTETRAHYDROPYRAN; SODIUM LAURETH SULFATE; BENZYL SALICYLATE; COCAMIDOPROPYLAMINE OXIDE; BENZYL ACETATE; SODIUM BENZOATE

Hi-Tech

Hi-Tech

Active Ingredient

Chloroxylenol 0.375%

Hi-Tech

Uses

- Antibacterial hand cleaner.
- Use in daycare, hospitals, nursing homes, physicians offices, dental offices and clinics

Hi-Tech

Warnings

- For external use only.
- Avoid contact with eyes.
- Children under the age of 6 should be supervised by an adult when using this product.
- Discontinue use is irritation or redness develops.
- If irritation persists for more than 72 hours, consult a physician.
- KEEP OUT OF REACH OF CHILDREN.

Hi-Tech

Directions

- Read the entire label before using this product.
- Dispense 1-2 pumps of product onto wet palm.
- Lather and rinse hands with clean water

Hi-Tech

Inactive Ingredients

Water, Sodium Lauryl lSulfate, Cocamide DEA, Cocamidopropyl betadine, Phenoxyethanol, Sodium Laureth Sulfate, Propylene Glycol, Fragrance, DMDM Hydantoin, Glycol Stearate, Laurimide DEA, Glycerine, Tocopheryl Acetate, D&C Green #5, FD&C Yellow #5.

Hi-Tech

Purpose

Antibacterial

Hi-Tech

Winning Hands Antibacterial

KEEP OUT OF REACH OF CHILDREN

Economical Hi Tech Antiseptic Hand

14104-00 Economical Hi Tech Antiseptic Hand